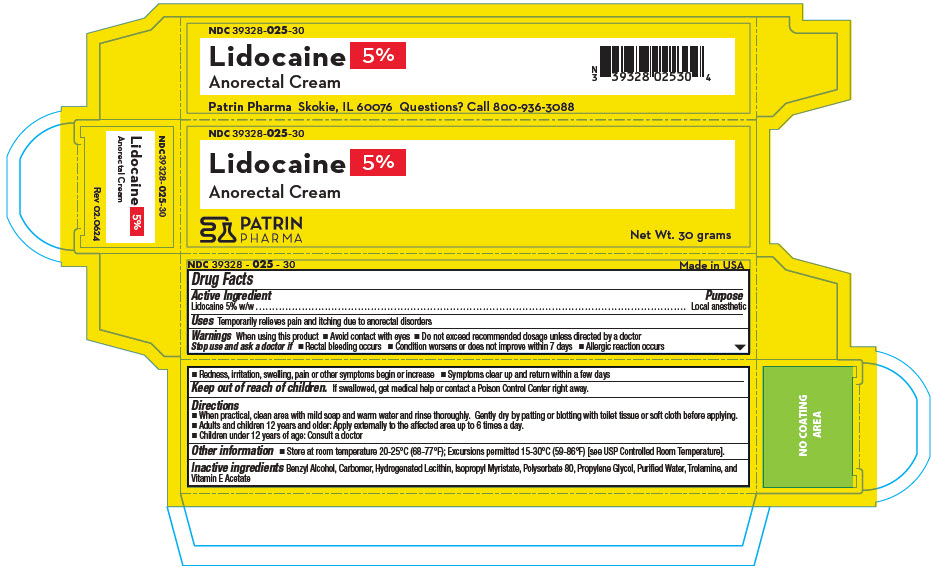 DRUG LABEL: Lidocaine Anorectal
NDC: 39328-025 | Form: CREAM
Manufacturer: Patrin Pharma, Inc
Category: otc | Type: HUMAN OTC DRUG LABEL
Date: 20241113

ACTIVE INGREDIENTS: Lidocaine 50 mg/1 g
INACTIVE INGREDIENTS: Benzyl Alcohol; CARBOMER HOMOPOLYMER TYPE C (ALLYL PENTAERYTHRITOL CROSSLINKED); HYDROGENATED SOYBEAN LECITHIN; Isopropyl Myristate; Polysorbate 80; Propylene Glycol; WATER; Trolamine; .ALPHA.-TOCOPHEROL ACETATE

Lidocaine 5% Anorectal Cream

Drug Facts

Active Ingredient

Lidocaine 5% w/w

Purpose

Local anesthetic

Uses

Temporarily relieves pain and itching due to anorectal disorders

Warnings

When using this product

- Avoid contact with eyes
- Do not exceed recommended dosage unless directed by a doctor

Stop use and ask a doctor if

- Rectal bleeding occurs
- Condition worsens or does not improve within 7 days
- Allergic reaction occurs
- Redness, irritation, swelling, pain or other symptoms begin or increase
- Symptoms clear up and return within a few days

Keep out of reach of children. If swallowed, get medical help or contact a Poison Control Center right away.

Directions

- When practical, clean area with mild soap and warm water and rinse thoroughly. Gently dry by patting or blotting with toilet tissue or soft cloth before applying.
- Adults and children 12 years and older: Apply externally to the affected area up to 6 times a day.
- Children under 12 years of age: Consult a doctor

Other information

- Store at room temperature 20–25°C (68–77°F); Excursions permitted 15–30°C (59–86°F) [see USP Controlled Room Temperature].

Inactive ingredients

Benzyl Alcohol, Carbomer, Hydrogenated Lecithin, Isopropyl Myristate, Polysorbate 80, Propylene Glycol, Purified Water, Trolamine, and Vitamin E Acetate

Questions?

Call 800-936-3088

PRINCIPAL DISPLAY PANEL - 30 gram Tube Carton

NDC 39328-025-30

Lidocaine
5%
Anorectal Cream

PATRIN
PHARMA

Net Wt. 30 grams